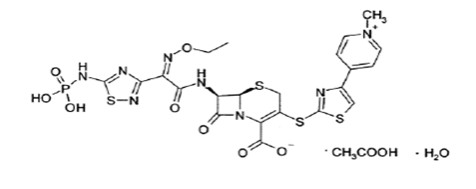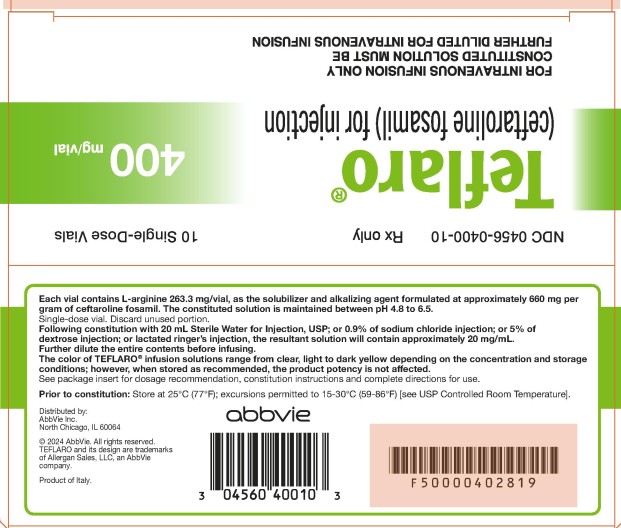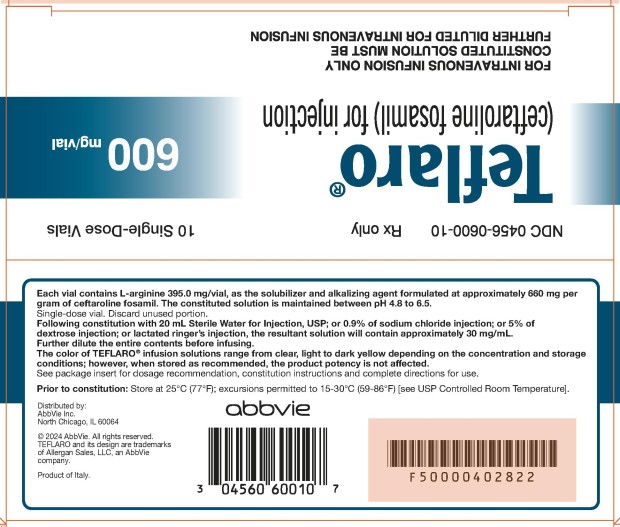 DRUG LABEL: Teflaro
NDC: 0456-0400 | Form: POWDER, FOR SOLUTION
Manufacturer: Allergan, Inc.
Category: prescription | Type: HUMAN PRESCRIPTION DRUG LABEL
Date: 20241120

ACTIVE INGREDIENTS: CEFTAROLINE FOSAMIL 400 mg/20 mL
INACTIVE INGREDIENTS: ARGININE 263.3 mg/20 mL

HIGHLIGHTS OF PRESCRIBING INFORMATION

These highlights do not include all the information needed to use TEFLARO safely and effectively. See full prescribing information for TEFLARO.
TEFLARO® (ceftaroline fosamil) for injection, for intravenous use
Initial U.S. Approval: 2010

1. INDICATIONS AND USAGE

Teflaro is a cephalosporin antibacterial indicated in adult and pediatric patients for the treatment of the following infection caused by designated susceptible bacteria:

- Acute bacterial skin and skin structure infections (ABSSSI) in adult and pediatric patients (at least 34 weeks gestational age and 12 days postnatal age) (1.1)
- Community-acquired bacterial pneumonia (CABP) in adult and pediatric patients 2 months of age and older (1.2)

To reduce the development of drug-resistant bacteria and maintain the effectiveness of Teflaro and other antibacterial drugs, Teflaro should be used only to treat or prevent infections that are proven or strongly suspected to be caused by bacteria. (1.3)

2. DOSAGE AND ADMINISTRATION

Dosage of Teflaro by Indication in Adult and Pediatric Patients (2.1, 2.2)

Indication | Age Range | Dosage | Infusion Time | Duration
Acute Bacterial Skin and Skin Structure Infections (ABSSSI) | 18 years and older | 600 mg every 12 hours | 5 to 60 minutes | 5 to 14 days
 | ≥2 years to < 18 years (> 33 kg) | 400 mg every 8 hours OR 600 mg every 12 hours | 5 to 60 minutes | 5 to 14 days
 | ≥2 years to < 18 years (≤ 33kg) | 12 mg/kg every 8 hours | 5 to 60 minutes | 5 to 14 days
 | 2 months to < 2 years | 8 mg/kg every 8 hours | 5 to 60 minutes | 5 to 14 days
 | 0* to < 2 months | 6 mg/kg every 8 hours | 30 to 60 minutes | 5 to 14 days

*Gestational age 34 weeks and older and postnatal age 12 days and older

Indication | Age Range | Dosage | Infusion Time | Duration
Community Acquired Bacterial Pneumonia (CABP) | 18 years and older | 600 mg every 12 hours | 5 to 60 minutes | 5 to 7 days
 | ≥2 years to < 18 years (> 33 kg) | 400 mg every 8 hours OR 600 mg every 12 hours | 5 to 60 minutes | 5 to 14 days
 | ≥2 years to < 18 years (≤ 33kg) | 12 mg/kg every 8 hours | 5 to 60 minutes | 5 to 14 days
 | 2 months to < 2 years | 8 mg/kg every 8 hours | 5 to 60 minutes | 5 to 14 days

- Dosage adjustment is required in adult patients with creatinine clearance (CrCl) < 50 mL/min and in End-stage Renal Disease (ESRD) including hemodialysis (2.3)
- There is insufficient information to recommend a dosage regimen for pediatric patients with CrCL < 50 mL/min/1.73 m^2 (2.3)

3. DOSAGE FORMS AND STRENGTHS

For Injection: 600 mg or 400 mg of sterile ceftaroline fosamil powder in single-dose 20 mL vials. The powder is constituted and further diluted for intravenous injection. (3)

4. CONTRAINDICATIONS

- Known serious hypersensitivity to ceftaroline or other members of the cephalosporin class. (4)

5. WARNINGS AND PRECAUTIONS

- Serious hypersensitivity (anaphylactic) reactions have been reported with beta-lactam antibacterial drugs, including Teflaro. If a hypersensitivity reaction occurs, discontinue Teflaro. (5.1)
- Clostridioides difficile-associated diarrhea (CDAD) has been reported with nearly all systemic antibacterial agents, including Teflaro. Evaluate if diarrhea occurs. (5.2)
- Neurological adverse reactions have been reported in patients treated with cephalosporins, including Teflaro. If neurological adverse reactions occur, consider discontinuing Teflaro or making appropriate dosage adjustments in patients with renal impairment. (2.3, 5.3)
- Direct Coombs’ test seroconversion has been reported with Teflaro. If anemia develops during or after therapy, a diagnostic workup for drug-induced hemolytic anemia should be performed and consideration given to discontinuation of Teflaro. (5.4)

6. ADVERSE REACTIONS

The most common adverse reactions occurring in >2% of adult patients and ≥3% of pediatric patients are diarrhea, nausea, and rash. Additional adverse reactions that occurred in ≥3% of pediatric patients include vomiting and pyrexia. (6.1)

To report SUSPECTED ADVERSE REACTIONS, contact AbbVie Inc. at 1-800-678-1605 or FDA at 1-800-FDA-1088 or www.fda.gov/medwatch..

FULL PRESCRIBING INFORMATION

1. INDICATIONS AND USAGE

1.1 Acute Bacterial Skin and Skin Structure Infections

Teflaro is indicated in adult and pediatric patients (at least 34 weeks gestational age and 12 days postnatal age) for the treatment of acute bacterial skin and skin structure infections (ABSSSI) caused by susceptible isolates of the following Gram-positive and Gram-negative microorganisms: Staphylococcus aureus (including methicillin-susceptible and -resistant isolates), Streptococcus pyogenes, Streptococcus agalactiae, Escherichia coli, Klebsiella pneumoniae, and Klebsiella oxytoca [see Dosage and Administration (2.2) and Use in Specific Populations (8.4)].

1.2 Community-Acquired Bacterial Pneumonia

Teflaro is indicated in adult and pediatric patients 2 months of age and older for the treatment of community-acquired bacterial pneumonia (CABP) caused by susceptible isolates of the following Gram-positive and Gram-negative microorganisms: Streptococcus pneumoniae (including cases with concurrent bacteremia), Staphylococcus aureus (methicillin-susceptible isolates only), Haemophilus influenzae, Klebsiella pneumoniae, Klebsiella oxytoca, and Escherichia coli.

1.3 Usage

To reduce the development of drug-resistant bacteria and maintain the effectiveness of Teflaro and other antibacterial drugs, Teflaro should be used to treat or prevent infections that are proven or strongly suspected to be caused by susceptible bacteria. Appropriate specimens for microbiological examination should be obtained in order to isolate and identify the causative pathogens and to determine their susceptibility to ceftaroline. When culture and susceptibility information are available, they should be considered in selecting or modifying antibacterial therapy. In the absence of such data, local epidemiology and susceptibility patterns may contribute to the empiric selection of therapy.

2. DOSAGE AND ADMINISTRATION

2.1 Recommended Dosage in Adult Patients

The recommended dosage of Teflaro is 600 mg administered every 12 hours by intravenous (IV) infusion over 5 to 60 minutes in patients ≥ 18 years of age. The duration of therapy should be guided by the severity and site of infection and the patient’s clinical and bacteriological progress.

The recommended dosage and administration by infection is described in Table 1.

Table 1: Dosage of Teflaro by Indication in Adults
Indication | Dosage | Frequency | Infusion Time | Recommended Duration of Treatment
Acute Bacterial Skin and Skin Structure Infections (ABSSSI) | 600 mg | Every 12 hours | 5 to 60 minutes | 5-14 days
Community-Acquired Bacterial Pneumonia (CABP) | 600 mg | Every 12 hours | 5 to 60 minutes | 5-7 days

2.2 Recommended Dosage in Pediatric Patients

The recommended dosage of Teflaro in pediatric patients is based on the age and weight of the child. The duration of therapy should be guided by the severity, site of infection and the patient’s clinical and bacteriological progress.

Pediatric Patients 2 Months of Age and Older

- For pediatric patients 2 months of age and older, Teflaro is administered every 8 hours by intravenous infusion over 5 to 60 minutes.
- Teflaro dosing regimen is dependent on the type of infection (ABSSSI, CABP). See dosing Table 2 below.

Table 2: Dosage of Teflaro by Indication in Pediatric Patients 2 Months of Age and Older
Indication | Age Range | Dosage and Frequency | Infusion time | Recommended Duration of Treatment
Acute Bacterial Skin and Skin Structure Infections (ABSSSI) OR Community-Acquired Bacterial Pneumonia (CABP) | 2 months to < 2 years | 8 mg/kg every 8 hours | 5 to 60 minutes | 5-14 days
 | > 2 years to < 18 years (< 33 kg) | 12 mg/kg every 8 hours
 | > 2 years to < 18 years (> 33 kg) | 400 mg every 8 hours OR 600 mg every 12 hours

Pediatric Patients Less Than 2 Months of Age

- Teflaro is administered every 8 hours by intravenous infusion over 30 to 60 minutes for patients less than 2 months of age.
- Teflaro dosing regimen is only recommended for patients with ABSSSI. See dosing Table 3 below.
- Concentrations of Teflaro in the cerebrospinal fluid have not been evaluated [see Use in Specific Populations (8.4)].
- There is no information for dosing Teflaro in infants less than 34 weeks gestational age and less than 12 days postnatal age.

Table 3: Dosage of Teflaro in Pediatric Patients less Than 2 Months of Age
Indication | Age Range | Dosage and Frequency | Infusion time | Recommended Duration of Treatment
Acute Bacterial Skin and Skin Structure Infections (ABSSSI) | 0* to < 2 months | 6 mg/kg every 8 hours | 30 to 60 minutes | 5-14 days

*Gestational age 34 weeks and older and postnatal age 12 days and older.

2.3 Dosage Adjustments in Patients with Renal Impairment

Adults: No dosage adjustment is required in adult patients with CrCL > 50 mL/min. The dose in adult patients should be adjusted when creatinine clearance (CrCL) is < 50 mL/min as shown below (see Table 4).

Table 4: Dosage of Teflaro in Adult Patients with Renal Impairment
Estimated CrCla (mL/min) | Recommended Dosage Regimen for Teflaro
> 50 | No dosage adjustment necessary
> 30 to ≤ 50 | 400 mg IV (over 5 to 60 minutes) every 12 hours
≥ 15 to ≤ 30 | 300 mg IV (over 5 to 60 minutes) every 12 hours
End-stage renal disease, including hemodialysisb | 200 mg IV (over 5 to 60 minutes) every 12 hoursc

a Creatinine clearance (CrCl) estimated using the Cockcroft-Gault formula.

b End-stage renal disease is defined as CrCl < 15 mL/min.

c Teflaro is hemodialyzable; thus Teflaro should be administered after hemodialysis on hemodialysis days.

Pediatrics: No dosage adjustment is required in pediatric patients with CrCL > 50 mL/min/1.73 m^2, estimated using the Schwartz equation. There is insufficient information to recommend a dosage regimen for pediatric patients with CrCL < 50 mL/min/1.73 m^2.

2.4 Preparation of Teflaro for Administration

Constitution of Teflaro Powder for Injection

Aseptic technique must be followed in preparing the infusion solution. The contents of Teflaro vial should be constituted with 20 mL Sterile Water for Injection, USP; or 0.9% of sodium chloride injection; or 5% of dextrose injection; or lactated ringer’s injection. Constitution time is less than 2 minutes. Mix gently to constitute and check to see that the contents have dissolved completely. The preparation of Teflaro solutions is summarized in Table 5.

Table 5: Preparation of Teflaro for Intravenous Use
Dosage Strength (mg) | Volume of Diluent To Be Added (mL) | Approximate Ceftaroline fosamil Concentration (mg/mL) | Amount to Be Withdrawn
400 | 20 | 20 | Adults: Total Volume Pediatric*: Volume based on age and weight
600 | 20 | 30 | Adults: Total Volume Pediatric*: Volume based on age and weight

* The recommended dosage of Teflaro is based on the age and weight of the child. See Table 2

Dilution of the Constituted Solution of Teflaro

The constituted solution must be further diluted in a range between 50 mL to 250 mL before intravenous infusion into patients. Use the same diluent used for constitution of the powder for this further dilution, unless sterile water for injection was used earlier. If sterile water for injection was used earlier, then appropriate infusion solutions include: 0.9% Sodium Chloride Injection, USP; 5% Dextrose Injection, USP; 2.5% Dextrose Injection, USP, and 0.45% Sodium Chloride Injection, USP; or Lactated Ringer’s Injection, USP.

Dilution of the Constituted Solution of Teflaro in the 50 mL Infusion Bags Only

Preparation of 600 mg of Teflaro dose in 50 mL infusion bag (for adult patients): Withdraw 20 mL of diluent from the infusion bag. Proceed to inject entire content of the Teflaro vial into the bag to provide a total volume of 50 mL. The resultant concentration is approximately 12 mg/mL.

Preparation of 400 mg of Teflaro dose in 50 mL infusion bag (for adult patients or pediatric patients weighing > 33 kg): Withdraw 20 mL of diluent from the infusion bag. Proceed to inject entire content of the Teflaro vial into the bag to provide a total volume of 50 mL. The resultant concentration is approximately 8 mg/mL.

Preparation of Teflaro dose in the infusion bag (for pediatric patients weighing ≤ 33 kg): The amount of solution withdrawn from the constituted Teflaro vial for pediatric patients weighing < 33 kg for dilution in the infusion bag will vary according to the weight and age of the child. The infusion solution concentration for administration should not exceed 12 mg/ml ceftaroline fosamil. Discard unused portion.

The color of Teflaro infusion solutions ranges from clear, light to dark yellow depending on the concentration and storage conditions. When stored as recommended, the product potency is not affected. Parenteral drug products should be inspected visually for particulate matter and discoloration prior to administration, whenever solution and container permit.

2.5 Storage of Constituted Solutions

Stability in Baxter® Mini-Bag Plus™: Solutions of Teflaro in concentrations ranging from 4 to 12 mg/mL in Baxter Mini-Bag Plus containers with 0.9% Sodium Chloride Injection may be stored for up to 6 hours at room temperature or for up to 24 hours at 2°C to 8°C (36°F to 46°F). Stability testing in the Baxter Mini-Bag Plus has solely been conducted on 50 mL and 100 mL containers (0.9% Sodium Chloride Injection).

Stability in Infusion Bag: Studies have shown that the constituted solution in the infusion bag should be used within 6 hours when stored at room temperature or within 24 hours when stored under refrigeration at 2 to 8º C (36 to 46º F).

2.6 Drug Compatibilities

The compatibility of Teflaro with other drugs has not been established. Teflaro should not be mixed with or physically added to solutions containing other drugs.

3. DOSAGE FORMS AND STRENGTHS

For Injection: Teflaro is supplied as 600 mg or 400 mg of pale yellowish-white to light yellow sterile ceftaroline fosamil (equivalent to 668 mg and 446 mg, respectively, of ceftaroline fosamil monoacetate monohydrate) powder in single-dose, 20 mL clear glass vials. The powder is constituted and further diluted for intravenous injection.

4. CONTRAINDICATIONS

Teflaro is contraindicated in patients with known serious hypersensitivity to ceftaroline or other members of the cephalosporin class. Anaphylaxis has been reported with ceftaroline.

5. WARNINGS AND PRECAUTIONS

5.1 Hypersensitivity Reactions

Serious and occasionally fatal hypersensitivity (anaphylactic) reactions and serious skin reactions have been reported in patients receiving beta-lactam antibacterial drugs. Before therapy with Teflaro is instituted, careful inquiry about previous hypersensitivity reactions to other cephalosporins, penicillins, or carbapenems should be made. Maintain clinical supervision if this product is to be given to a penicillin- or other beta-lactam-allergic patient, because cross sensitivity among beta-lactam antibacterial agents has been clearly established.

If an allergic reaction to Teflaro occurs, discontinue Teflaro and institute appropriate treatment and supportive measures.

5.2 Clostridioides difficile-Associated Diarrhea

Clostridioides difficile-associated diarrhea (CDAD) has been reported for nearly all systemic antibacterial agents, including Teflaro, and may range in severity from mild diarrhea to fatal colitis.

Treatment with antibacterial agents alters the normal flora of the colon and may permit overgrowth of C. difficile.

C. difficile produces toxins A and B which contribute to the development of CDAD. Hypertoxin-producing strains of C. difficile cause increased morbidity and mortality, as these infections can be refractory to antimicrobial therapy and may require colectomy. CDAD must be considered in all patients who present with diarrhea following antibiotic use. Careful medical history is necessary because CDAD has been reported to occur more than 2 months after the administration of antibacterial agents.

If CDAD is suspected or confirmed, antibacterials not directed against C. difficile should be discontinued, if possible. Appropriate fluid and electrolyte management, protein supplementation, antibiotic treatment of C. difficile, and surgical evaluation should be instituted as clinically indicated [see Adverse Reactions (6.1)].

5.3 Neurological Adverse Reactions

Neurological adverse reactions have been reported during postmarketing surveillance in patients treated with cephalosporins, including Teflaro. These reactions include encephalopathy and seizures [see Adverse Reactions (6.2)]. Most cases occurred in patients with renal impairment who did not receive appropriate dosage adjustment. The neurological adverse reactions were reversible and resolved after discontinuation of Teflaro or after hemodialysis. If neurological adverse reactions associated with Teflaro therapy occur, consider discontinuing Teflaro or making appropriate dosage adjustments in patients with renal impairment [see Dosage and Administration (2.3)].

5.4 Direct Coombs’ Test Seroconversion

Seroconversion from a negative to a positive direct Coombs’ test result occurred in 120/1114 (10.8%) of adult patients receiving Teflaro and 49/1116 (4.4%) of patients receiving comparator drugs in the four pooled adult Phase 3 trials.

In the pooled adult Phase 3 CABP trials, 51/520 (9.8%) of Teflaro-treated patients compared to 24/534 (4.5%) of ceftriaxone-treated patients seroconverted from a negative to a positive direct Coombs’ test result. No adverse reactions representing hemolytic anemia were reported in any treatment group.

Seroconversion from a negative to a positive direct Coombs’ test result occurred in 42/234 (17.9%) of children receiving Teflaro and 3/93 (3.2%) of patients receiving comparator drugs in the three pooled pediatric trials. No adverse reactions representing hemolytic anemia were reported in any treatment group.

If anemia develops during or after treatment with Teflaro, drug-induced hemolytic anemia should be considered. Diagnostic studies including a direct Coombs’ test, should be performed. If drug-induced hemolytic anemia is suspected, discontinuation of Teflaro should be considered and supportive care should be administered to the patient (i.e. transfusion) if clinically indicated.

5.5 Development of Drug-Resistant Bacteria

Prescribing Teflaro in the absence of a proven or strongly suspected bacterial infection or a prophylactic indication is unlikely to provide benefit to the patient and increases the risk of the development of drug-resistant bacteria.

6. ADVERSE REACTIONS

The following serious adverse reactions are described in greater detail in the Warnings and Precautions section

- Hypersensitivity Reactions [see Warnings and Precautions (5.1)]
- Clostridioides difficile-Associated diarrhea [see Warnings and Precautions (5.2)]
- Neurological Adverse Reactions [see Warnings and Precautions (5.3)]
- Direct Coombs’ Test Seroconversion [see Warnings and Precautions (5.4)]

6.1 Clinical Trials Experience

Because clinical trials are conducted under widely varying conditions, adverse reaction rates observed in clinical trials of a drug cannot be compared directly to rates from clinical trials of another drug and may not reflect rates observed in practice.

Adult Patients

Teflaro was evaluated in four controlled comparative Phase 3 clinical trials (two in ABSSSI and two in CABP) which included 1300 adult patients treated with Teflaro (600 mg administered by IV over 1 hour every 12h) and 1297 patients treated with comparator (vancomycin plus aztreonam or ceftriaxone) for a treatment period up to 21 days. The median age of patients treated with Teflaro was 54 years, ranging between 18 and 99 years old. Patients treated with Teflaro were predominantly male (63%) and Caucasian (82%).

Serious Adverse Reactions and Adverse Reactions Leading to Discontinuation

In the four pooled adult Phase 3 clinical trials, serious adverse reactions (SARs) occurred in 98/1300 (7.5%) of patients receiving Teflaro and 100/1297 (7.7%) of patients receiving comparator drugs. Treatment discontinuation due to adverse reactions occurred in 35/1300 (2.7%) of patients receiving Teflaro and 48/1297 (3.7%) of patients receiving comparator drugs with the most common adverse reactions leading to discontinuation being hypersensitivity for both treatment groups at a rate of 0.3% in the Teflaro group and 0.5% in comparator group.

Most Common Adverse Reactions

No adverse reactions occurred in greater than 5% of adult patients receiving Teflaro. The most common adverse reactions occurring in > 2% of patients receiving Teflaro in the pooled adult phase 3 clinical trials were diarrhea, nausea, and rash.

Table 6 lists adverse reactions occurring in ≥ 2% of patients receiving Teflaro in the pooled adult Phase 3 clinical trials.

Table 6: Adverse Reactions Occurring in ≥ 2% of Patients Receiving Teflaro in the Pooled Adult Phase 3 Clinical Trials
Adverse Reactions | Pooled Phase 3 Clinical Trials (four trials, two in ABSSSI and two in CABP)
 | Teflaro (N=1300) | Pooled Comparatorsa (N=1297)
Gastrointestinal Disorders
Diarrhea | 5 % | 3 %
Nausea | 4 % | 4 %
Constipation | 2 % | 2 %
Vomiting | 2 % | 2 %
Laboratory Investigations
Increased transaminases | 2% | 3 %
Metabolism and Nutrition disorders
Hypokalemia | 2 % | 3 %
Skin and Subcutaneous Tissue Disorders
Rash | 3% | 2%
Vascular Disorders
Phlebitis | 2% | 1%

a Comparators included vancomycin 1 gram IV every 12h plus aztreonam 1 gram IV every 12h in the Phase 3 ABSSSI trials, and ceftriaxone 1 gram IV every 24h in the Phase 3 CABP trials.

Other Adverse Reactions Observed During Clinical Trials of Teflaro

Following is a list of additional adverse reactions reported by the 1740 adult patients who received Teflaro in any clinical trial with incidences less than 2%.

Blood and lymphatic system disorders - Anemia, Eosinophilia, Neutropenia, Thrombocytopenia

Cardiac disorders - Bradycardia, Palpitations

Gastrointestinal disorders - Abdominal pain

General disorders and administration site conditions - Pyrexia

Hepatobiliary disorders - Hepatitis

Immune system disorders - Hypersensitivity, Anaphylaxis

Infections and infestations - Clostridioides difficile colitis

Metabolism and nutrition disorders - Hyperglycemia, Hyperkalemia

Nervous system disorders - Dizziness, Convulsion

Renal and urinary disorders - Renal failure

Skin and subcutaneous tissue disorders - Urticaria

Pediatric Patients

Teflaro was evaluated in three clinical trials (one in ABSSSI and two in CABP) which included 257 pediatric patients 2 months to < 18 years of age treated with Teflaro, and 102 patients treated with comparator agents for a treatment period up to 21 days. In two trials, one in ABSSSI and one in CABP, the dose was selected to result in exposures comparable to adult exposure with 600 mg administered by IV infusion every 12h. In an additional pediatric trial in complicated CABP the dose was higher. The median age of pediatric patients treated with Teflaro was 5 years, ranging from 2 months to < 18 years of age. Patients treated with Teflaro were predominantly male (55%) and Caucasian (92%).

A single study enrolled 11 pediatric patients with a gestational age of ≥34 weeks and a postnatal age of 12 days to less than 2 months of age. The safety findings were similar to those observed in adult and pediatric patients 2 months of age and older.

Serious Adverse Reactions and Adverse Reactions Leading to Discontinuation

In the three pooled pediatric clinical trials, SARs occurred in 10/257 (4%) of patients receiving Teflaro and 3/102 (3%) of patients receiving comparator drugs. Treatment discontinuation due to adverse reactions occurred in 10/257 (3.9%) of patients receiving Teflaro and 2/102 (2%) of patients receiving comparator drugs with the most common adverse reaction leading to discontinuation being rash in 2/257 (0.8%) of patients treated with Teflaro.

Most Common Adverse Reactions

No adverse reactions occurred in greater than 8% of pediatric patients receiving Teflaro. The most common adverse reactions occurring in ≥ 3% of patients receiving Teflaro in the pooled pediatric clinical trials were diarrhea, nausea, vomiting, pyrexia and rash.

Table 7 lists adverse reactions occurring in ≥ 3% of patients receiving Teflaro in the pooled pediatric clinical trials.

Table 7: Adverse Reactions Occurring in ≥ 3% of Patients Receiving Teflaro in the Pooled Pediatric Clinical Trials
Adverse Reactions | Pooled Pediatric Clinical Trials (three trials, one in ABSSSI and two in CABP)
 | Teflaro (N=257) | Pooled Comparatorsa (N=102)
Gastrointestinal Disorders
Diarrhea | 8 % | 10 %
Nausea | 3 % | 1 %
Vomiting | 5 % | 12 %
General and Administrative Site disorders
Pyrexia | 3% | 2 %
Skin and Subcutaneous Tissue Disorders
Rash | 7% | 4%

a Comparators included vancomycin or cefazolin with or without aztreonam in the ABSSSI trial and ceftriaxone alone or ceftriaxone plus vancomycin in the CABP trials

Following is a list of additional adverse reactions reported by the 257 patients who received Teflaro in the pediatric clinical trials with incidences less than 3%.

Investigations – Alanine aminotransferase increased, Aspartate aminotransferase increased

Nervous system disorders – Headache

Skin and subcutaneous tissue disorders- Pruritus

6.2 Postmarketing Experience

The following adverse reactions have been identified during post approval use of Teflaro in adult patients. Because these adverse reactions are reported voluntarily from a population of uncertain size, it is not always possible to reliably estimate their frequency or establish a causal relationship to drug exposure.

Blood and lymphatic system disorders: Agranulocytosis, leukopenia, eosinophilic pneumonia.

Nervous system disorders: Encephalopathy, seizures [see Warnings and Precautions (5.3)]

8. USE IN SPECIFIC POPULATIONS

8.1 Pregnancy

Risk Summary

There are no adequate studies with Teflaro in pregnant women that informed any drug associated risks. The background risk of major birth defects and miscarriage for the indicated population is unknown. The background risk of major birth defects is 2-4% and of miscarriage is 15-20% of clinically recognized pregnancies within the general population.

In developmental toxicity studies conducted in animals, no malformations or other adverse developmental effects were observed in offspring of rats exposed to Teflaro at up to 4 times the maximum recommended human dose (MRHD) during the period of organogenesis through lactation. In rabbits exposed to Teflaro during organogenesis at levels approximately equal to the MRHD, no drug-induced fetal malformations were observed despite maternal toxicity.

Data

Animal Data

Developmental toxicity studies performed with ceftaroline fosamil in rats at IV doses up to 300 mg/kg demonstrated no maternal toxicity and no effects on the fetus. A separate toxicokinetic study showed that ceftaroline exposure in rats (based on AUC) at this dose level was approximately 4 times the exposure in humans given 600 mg every 12 hours. There were no drug-induced malformations in the offspring of rabbits given IV doses of 25, 50, and 100 mg/kg, despite maternal toxicity. Signs of maternal toxicity appeared secondary to the sensitivity of the rabbit gastrointestinal system to broad-spectrum antibacterials and included changes in fecal output in all groups and dose-related reductions in body weight gain and food consumption at > 50 mg/kg; these were associated with an increase in spontaneous abortion at 50 and 100 mg/kg. The highest dose was also associated with maternal moribundity and mortality. An increased incidence of a common rabbit skeletal variation, angulated hyoid alae, was also observed at the maternally toxic doses of 50 and 100 mg/kg. A separate toxicokinetic study showed that ceftaroline exposure in rabbits (based on AUC) was approximately 0.4 times the exposure in humans given 600 mg every 12 hours at 25 mg/kg and 0.7 times the human exposure at 50 mg/kg.

Ceftaroline fosamil did not affect the postnatal development or reproductive performance of the offspring of rats given IV doses up to 450 mg/kg/day. Results from a toxicokinetic study conducted in pregnant rats with doses up to 300 mg/kg suggest that exposure was ≥ 4 times the exposure in humans given 600 mg every 12 hours.

8.2 Lactation

Risk Summary

No data is available regarding the presence of ceftaroline in human milk, the effects of ceftaroline on breastfed infants, or the effects on milk production.

The developmental and health benefits of breastfeeding should be considered along with the mother’s clinical need for Teflaro and any potential adverse effects on the breastfed child from Teflaro or from the underlying maternal condition.

8.4 Pediatric Use

The safety and effectiveness of Teflaro in the treatment of ABSSSI have been established in pediatric patients (at least 34 weeks gestational age and 12 days postnatal age).

The safety and effectiveness of Teflaro in the treatment of CABP have been established in the age groups 2 months to less than 18 years old.

Use of Teflaro in these age groups is supported by evidence from adequate and well-controlled studies of Teflaro in adults with additional pharmacokinetic and safety data in pediatric patients 2 months of age and older with ABSSSI or CABP [see Clinical Studies (14.1 and 14.2)]. Use of Teflaro in pediatric patients less than 2 months of age was supported by pharmacokinetic and safety data in 11 infants at least 34 weeks gestational age and 12 days postnatal age. In these infants, concentrations of Teflaro in the cerebrospinal fluid were not evaluated [see Adverse Reactions (6.1), Clinical Pharmacology (12.3) and Clinical Studies (14.2)].

Results from the clinical studies in pediatric patients show that Teflaro demonstrated a safety profile that was comparable with treatment of ABSSSI and CABP in adults at the clinical dosages studied.

Safety and effectiveness of Teflaro in pediatric patients less than 34 weeks gestational age and less than 12 days postnatal age for the treatment of ABSSSI have not been established.

Safety and effectiveness of Teflaro in pediatric patients below the age of 2 months for the treatment of CABP have not been established as no data are available.

8.5 Geriatric Use

Of the 1300 adult patients treated with Teflaro in the Phase 3 ABSSSI and CABP trials, 397 (30.5%) were ≥ 65 years of age. The clinical cure rates in the Teflaro group (Clinically Evaluable [CE] Population) were similar in patients ≥ 65 years of age compared with patients < 65 years of age in both the ABSSSI and CABP trials.

The adverse reaction profiles in patients ≥ 65 years of age and in patients < 65 years of age were similar. The percentage of patients in the Teflaro group who had at least one adverse reaction was 52.4% in patients ≥ 65 years of age and 42.8% in patients < 65 years of age for the two indications combined.

Ceftaroline is excreted primarily by the kidney, and the risk of adverse reactions may be greater in patients with impaired renal function. Because elderly patients are more likely to have decreased renal function, care should be taken in dose selection in this age group and it may be useful to monitor renal function. Elderly subjects had greater ceftaroline exposure relative to non-elderly subjects when administered the same single dose of Teflaro. However, higher exposure in elderly subjects was mainly attributed to age-related changes in renal function. Dosage adjustment for elderly patients should be based on renal function [see Dosage and Administration (2.2) and Clinical Pharmacology (12.3)].

8.6 Patients with Renal Impairment

Dosage adjustment is required in adult patients with moderate (CrCl > 30 to ≤ 50 mL/min) or severe (CrCl ≥ 15 to ≤ 30 mL/min) renal impairment and in patients with end-stage renal disease (ESRD – defined as CrCl < 15 mL/min), including patients on hemodialysis (HD). There is insufficient information to recommend a dosage regimen for pediatric patients with CrCl < 50 ml/min [see Dosage and Administration (2.2) and Clinical Pharmacology (12.3)].

10. OVERDOSAGE

Teflaro overdosage has occurred in patients with renal impairment. Reactions have included neurological sequelae, including encephalopathy [see Dosage and Administration (2.3), Warnings and Precautions (5.3) and Adverse Reactions (6.2)].

In the event of overdose, Teflaro should be discontinued and general supportive treatment given. Ceftaroline can be removed by hemodialysis. In subjects with ESRD administered 400 mg of Teflaro, the mean total recovery of ceftaroline in the dialysate following a 4-hour hemodialysis session started 4 hours after dosing was 76.5 mg (21.6% of the dose). However, no information is available on the use of hemodialysis to treat overdosage [see Clinical Pharmacology (12.3)].

11. DESCRIPTION

TEFLARO (ceftaroline fosamil) for injection, is a sterile, semi-synthetic, prodrug of the cephalosporin antibacterial class of beta-lactams (β-lactams) for intravenous use. Chemically, the prodrug, ceftaroline fosamil monoacetate monohydrate is (6R,7R)-7-{(2Z)-2-(ethoxyimino)-2-[5-(phosphonoamino)-1,2,4-thiadiazol-3-yl]acetamido}-3-{[4-(1-methylpyridin-1-ium-4-yl)-1,3-thiazol-2-yl]sulfanyl}-8-oxo-5-thia-1-azabicyclo[4.2.0]oct-2-ene-2-carboxylate monoacetate monohydrate. Its molecular weight is 762.75. The empirical formula is C22H21N8O8PS4.C2H4O2.H2O.

Figure 1: Chemical structure of ceftaroline fosamil

Teflaro vials contain either 600 mg or 400 mg of anhydrous ceftaroline fosamil (equivalent to 668 mg and 446 mg, respectively, of ceftaroline fosamil monoacetate monohydrate). The powder for injection is formulated from ceftaroline fosamil monoacetate monohydrate, a pale yellowish-white to light yellow sterile powder. Each vial of 400 mg of anhydrous ceftaroline fosamil includes inactive ingredient L-arginine 263.3 mg/vial as the solubilizer and alkalizing agent. Each vial of 600 mg of anhydrous ceftaroline fosamil includes inactive ingredient L-arginine 395.0 mg/vial as the solubilizer and alkalizing agent. All references to ceftaroline activity are expressed in terms of the prodrug, ceftaroline fosamil. The powder is constituted for IV injection [see Dosage and Administration (2.3)].

The pH of the constituted solution is pH 4.8 to 6.5.

12. CLINICAL PHARMACOLOGY

12.1 Mechanism of Action

Ceftaroline is a cephalosporin antibacterial drug [see Microbiology (12.4)].

12.2 Pharmacodynamics

As with other beta-lactam antimicrobial agents, the time that unbound plasma concentration of ceftaroline exceeds the minimum inhibitory concentration (MIC) of the infecting organism has been shown to best correlate with efficacy in a neutropenic murine thigh infection model with S. aureus and S. pneumoniae.

Exposure-response analysis of Phase 2/3 ABSSSI trials supports the recommended dosage regimen of Teflaro 600 mg every 12 hours by IV infusion over 1 hour. For Phase 3 CABP trials, an exposure-response relationship could not be identified due to the limited range of ceftaroline exposures in the majority of patients.

Cardiac Electrophysiology

In a randomized, positive- and placebo-controlled crossover thorough QTc study, 54 healthy subjects were each administered a single dose of Teflaro 1500 mg, placebo, and a positive control by IV infusion over 1 hour. At the 1500 mg dose of Teflaro, no significant effect on QTc interval was detected at peak plasma concentration or at any other time.

12.3 Pharmacokinetics

The mean pharmacokinetic parameters of ceftaroline in healthy adults (n=6) with normal renal function after single and multiple 1-hour IV infusions of 600 mg ceftaroline fosamil administered every 12 hours are summarized in Table 8. Pharmacokinetic parameters were similar for single and multiple dose administration.

Table 8: Mean (Standard Deviation) Pharmacokinetic Parameters of Ceftaroline IV in Healthy Adults
Parameter | Single 600 mg Dose Administered as a 1-Hour Infusion (n=6) | Multiple 600 mg Doses Administered Every 12 Hours as 1-Hour Infusions for 14 Days (n=6)
Cmax (mcg/mL) | 19.0 (0.71) | 21.3 (4.10)
Tmax (h) a | 1.00 (0.92-1.25) | 0.92 (0.92-1.08)
AUC (mcg•h/mL) b | 56.8 (9.31) | 56.3 (8.90)
T 1/2 (h) | 1.60 (0.38) | 2.66 (0.40)
CL (L/h) | 9.58 (1.85) | 9.60 (1.40)
a Reported as median (range)
b AUC0-∞, for single-dose administration; AUC0-tau, for multiple-dose administration; Cmax, maximum observed concentration; Tmax, time of Cmax; AUC0-∞, area under concentration-time curve from time 0 to infinity; AUC0-tau, area under concentration-time curve over dosing interval (0-12 hours); T1/2, terminal elimination half-life; CL, plasma clearance

The Cmax and AUC of ceftaroline increase approximately in proportion to dose within the single dose range of 50 to 1000 mg. No appreciable accumulation of ceftaroline is observed following multiple IV infusions of 600 mg administered every 12 hours for up to 14 days in healthy adults with normal renal function.

The systemic exposure (AUC), T1/2, and clearance of ceftaroline were similar following administration of 600 mg ceftaroline fosamil in a volume of 50 mL to healthy subjects every 8 hours for 5 days as a 5-minute or 60-minute infusion, and the Tmax of ceftaroline occurred about 5 minutes after the end of the ceftaroline fosamil infusion for both infusion durations. The mean (SD) Cmax of ceftaroline was 32.5 (4.82) mcg/mL for the 5-minute infusion duration (n=11) and 17.4 (3.87) mcg/mL for the 60-minute infusion duration (n=12).

Distribution

The average binding of ceftaroline to human plasma proteins is approximately 20% and decreases slightly with increasing concentrations over 1-50 mcg/mL (14.5-28.0%). The median (range) steady-state volume of distribution of ceftaroline in healthy adult males (n=6) following a single 600 mg IV dose of radiolabeled ceftaroline fosamil was 20.3 L (18.3-21.6 L), similar to extracellular fluid volume.

Elimination

Metabolism

Ceftaroline fosamil is the water-soluble prodrug of the bioactive ceftaroline. Ceftaroline fosamil is converted into bioactive ceftaroline in plasma by a phosphatase enzyme and concentrations of the prodrug are measurable in plasma primarily during IV infusion. Hydrolysis of the beta-lactam ring of ceftaroline occurs to form the microbiologically inactive, open-ring metabolite ceftaroline M-1. The mean (SD) plasma ceftaroline M-1 to ceftaroline AUC0-∞ ratio following a single 600 mg IV infusion of ceftaroline fosamil in healthy adults (n=6) with normal renal function is 28% (3.1%).

When incubated with pooled human liver microsomes, ceftaroline was metabolically stable (< 12% metabolic turnover), indicating that ceftaroline is not a substrate for hepatic CYP450 enzymes.

Excretion

Ceftaroline and its metabolites are primarily eliminated by the kidneys. Following administration of a single 600 mg IV dose of radiolabeled ceftaroline fosamil to healthy male adults (n=6), approximately 88% of radioactivity was recovered in urine and 6% in feces within 48 hours. Of the radioactivity recovered in urine approximately 64% was excreted as ceftaroline and approximately 2% as ceftaroline M-1. The mean (SD) renal clearance of ceftaroline was 5.56 (0.20) L/h, suggesting that ceftaroline is predominantly eliminated by glomerular filtration.

Specific Populations

Patients with Renal Impairment

Following administration of a single 600 mg IV dose of Teflaro, the geometric mean AUC0-∞ of ceftaroline in subjects with mild (CrCl > 50 to ≤ 80 mL/min, n=6) or moderate (CrCl > 30 to ≤ 50 mL/min, n=6) renal impairment was 19% and 52% higher, respectively, compared to healthy subjects with normal renal function (CrCl > 80 mL/min, n=6). Following administration of a single 400 mg IV dose of Teflaro, the geometric mean AUC0-∞ of ceftaroline in subjects with severe (CrCl ≥ 15 to ≤30 mL/min, n=6) renal impairment was 115% higher compared to healthy subjects with normal renal function (CrCl > 80 mL/min, n=6). Dosage adjustment is recommended in patients with moderate and severe renal impairment [see Dosage and Administration (2.2)].

A single 400 mg dose of Teflaro was administered to subjects with ESRD (n=6) either 4 hours prior to or 1 hour after hemodialysis (HD). The geometric mean ceftaroline AUC0-∞ following the post-HD infusion was 167% higher compared to healthy subjects with normal renal function (CrCl > 80 mL/min, n=6). The mean recovery of ceftaroline in the dialysate following a 4-hour HD session was 76.5 mg, or 21.6% of the administered dose. Dosage adjustment is recommended in patients with ESRD (defined as CrCL < 15 mL/min), including patients on HD [see Dosage and Administration (2.2)].

Patients with Hepatic Impairment

The pharmacokinetics of ceftaroline in patients with hepatic impairment have not been established. As ceftaroline does not appear to undergo significant hepatic metabolism, the systemic clearance of ceftaroline is not expected to be significantly affected by hepatic impairment.

Geriatric Patients

Following administration of a single 600 mg IV dose of Teflaro to healthy elderly subjects (≥ 65 years of age, n=16), the geometric mean AUC0-∞ of ceftaroline was ~33% higher compared to healthy young adult subjects (18-45 years of age, n=16). The difference in AUC0-∞ was mainly attributable to age-related changes in renal function. Dosage adjustment for Teflaro in elderly patients should be based on renal function [see Dosage and Administration (2.2)].

Pediatric Patients

The pharmacokinetics of ceftaroline were evaluated in adolescent patients (ages 12 to 17, n=7) with normal renal function following administration of a single 8 mg/kg IV dose of Teflaro (or 600 mg for subjects weighing > 75 kg). The mean plasma clearance and terminal phase volume of distribution for ceftaroline in adolescent subjects were similar to healthy adults (n=6) with normal renal function in a separate study following administration of a single 600 mg IV dose. However, the mean Cmax and AUC0-∞ for ceftaroline in adolescent subjects who received a single 8 mg/kg dose were 10% and 23% less than in healthy adult subjects who received a single 600 mg IV dose. The population pharmacokinetic analyses demonstrated that the pharmacokinetics of ceftaroline in pediatric patients from 2 months to < 18 years of age were similar to those in adult patients after accounting for weight and maturational changes. No clinically significant differences in ceftaroline AUC were predicted in patients from 12 days to 2 months postnatal age and with ≥34 weeks of gestational age compared to adults and pediatric patients 2 months of age and older when given the approved recommended dosage for each patient population [see Adverse Reactions (6), Use in Specific Populations (8.4) and Clinical Studies (14)].

Gender

Following administration of a single 600 mg IV dose of Teflaro to healthy elderly males (n=10) and females (n=6) and healthy young adult males (n=6) and females (n=10), the mean Cmax and AUC0-∞ for ceftaroline were similar between males and females, although there was a trend for higher Cmax (17%) and AUC0-∞ (6-15%) in female subjects. Population pharmacokinetic analysis did not identify any significant differences in ceftaroline AUC0-tau based on gender in Phase 2/3 patients with ABSSSI or CABP. No dose adjustment is recommended based on gender.

Race

A population pharmacokinetic analysis was performed to evaluate the impact of race on the pharmacokinetics of ceftaroline using data from Phase 2/3 adult ABSSSI and CABP trials. No significant differences in ceftaroline AUC0-tau was observed across White (n=35), Hispanic (n=34), and Black (n=17) race groups for ABSSSI patients. Patients enrolled in CABP trials were predominantly categorized as White (n=115); thus there were too few patients of other races to draw any conclusions. No dosage adjustment is recommended based on race.

Drug Interactions Studies

No clinical drug-drug interaction studies have been conducted with Teflaro. There is minimal potential for drug-drug interactions between Teflaro and CYP450 substrates, inhibitors, or inducers; drugs known to undergo active renal secretion; and drugs that may alter renal blood flow.

In vitro studies in human liver microsomes indicate that ceftaroline does not inhibit the major cytochrome P450 isoenzymes CYP1A1, CYP1A2, CYP2A6, CYP2B6, CYP2C8, CYP2C9, CYP2C19, CYP2D6, CYP2E1 and CYP3A4. In vitro studies in human hepatocytes also demonstrate that ceftaroline and its inactive open-ring metabolite are not inducers of CYP1A2, CYP2B6, CYP2C8, CYP2C9, CYP2C19, or CYP3A4/5. Therefore, Teflaro is not expected to inhibit or induce the clearance of drugs that are metabolized by these metabolic pathways in a clinically relevant manner.

Population pharmacokinetic analysis did not identify any clinically relevant differences in ceftaroline exposure (Cmax and AUC0-tau) in Phase 2/3 patients with ABSSSI or CABP who were taking concomitant medications that are known inhibitors, inducers, or substrates of the cytochrome P450 system; anionic or cationic drugs known to undergo active renal secretion; and vasodilator or vasoconstrictor drugs that may alter renal blood flow.

12.4 Microbiology

Mechanism of Action
Ceftaroline is a cephalosporin antibacterial drug with in vitro activity against Gram-positive and -negative bacteria. The bactericidal action of ceftaroline is mediated through binding to essential penicillin-binding proteins (PBPs). Ceftaroline is bactericidal against S. aureus due to its affinity for PBP2a and against Streptococcus pneumoniae due to its affinity for PBP2x.

Resistance
Ceftaroline is not active against Gram-negative bacteria producing extended spectrum beta-lactamases (ESBLs) from the TEM, SHV or CTX-M families, serine carbapenemases (such as KPC), class B metallo-beta-lactamases, or class C (AmpC cephalosporinases). Although cross-resistance may occur, some isolates resistant to other cephalosporins may be susceptible to ceftaroline.

Interaction with Other Antimicrobials
In vitro studies have not demonstrated any antagonism between ceftaroline or other commonly used antibacterial agents (e.g., vancomycin, linezolid, daptomycin, levofloxacin, azithromycin, amikacin, aztreonam, tigecycline, and meropenem).

Antimicrobial Activity
Ceftaroline has been shown to be active against most of the following bacteria, both in vitro and in clinical infections [see Indications and Usage (1)].

Skin Infections
Gram-positive Bacteria
Staphylococcus aureus (including methicillin-susceptible and -resistant isolates)
Streptococcus pyogenes
Streptococcus agalactiae

Gram-negative Bacteria
Escherichia coli
Klebsiella pneumoniae
Klebsiella oxytoca

Community-Acquired Bacterial Pneumonia (CABP)
Gram-positive Bacteria
Streptococcus pneumoniae
Staphylococcus aureus (methicillin-susceptible isolates only)

Gram-negative Bacteria
Haemophilus influenzae
Klebsiella pneumoniae
Klebsiella oxytoca
Escherichia coli

The following in vitro data are available, but their clinical significance is unknown. At least 90 percent of the following bacteria exhibit an in vitro minimum inhibitory concentration (MIC) less than or equal to the susceptible breakpoint for ceftaroline against isolates of similar genus or organism group. However, the efficacy of ceftaroline in treating clinical infections due to these bacteria has not been established in adequate and well-controlled clinical trials.

Gram-positive Bacteria
Streptococcus dysgalactiae

Gram-negative Bacteria
Citrobacter koseri
Citrobacter freundii
Enterobacter cloacae
Enterobacter aerogenes
Moraxella catarrhalis
Morganella morganii
Proteus mirabilis
Haemophilus parainfluenzae

Susceptibility Test Methods

For specific information regarding susceptibility test interpretive criteria and associated test methods and quality control standards recognized by FDA for this drug, please see: https://www.fda.gov/STIC

13. NONCLINICAL TOXICOLOGY

13.1 Carcinogenesis, Mutagenesis, Impairment of Fertility

Long-term carcinogenicity studies have not been conducted with ceftaroline. Ceftaroline fosamil did not show evidence of mutagenic activity in in vitro tests that included a bacterial reverse mutation assay and the mouse lymphoma assay. Ceftaroline was not mutagenic in an in vitro mammalian cell assay. In vivo, ceftaroline fosamil did not induce unscheduled DNA synthesis in rat hepatocytes and did not induce the formation of micronucleated erythrocytes in mouse or rat bone marrow. Both ceftaroline fosamil and ceftaroline were clastogenic in the absence of metabolic activation in an in vitro chromosomal aberration assays, but not in the presence of metabolic activation.

IV injection of ceftaroline fosamil had no adverse effects on fertility of male and female rats given up to
450 mg/kg. This is approximately 4-fold higher than the maximum recommended human dose based on body surface area.

14. CLINICAL STUDIES

14.1 Acute Bacterial Skin and Skin Structure Infections (ABSSSI)

Adult Patients

A total of 1396 adults with clinically documented complicated skin and skin structure infection were enrolled in two identical randomized, multi-center, multinational, double-blind, non-inferiority trials (Trials 1 and 2) comparing Teflaro (600 mg administered IV over 1 hour every 12 hours) to vancomycin plus aztreonam (1 g vancomycin administered IV over 1 hour followed by 1 g aztreonam administered IV over 1 hour every 12 hours). Treatment duration was 5 to 14 days. A switch to oral therapy was not allowed. The Modified Intent-to-Treat (MITT) population included all patients who received any amount of study drug according to their randomized treatment group. The Clinically Evaluable (CE) population included patients in the MITT population who demonstrated sufficient adherence to the protocol.

To evaluate the treatment effect of ceftaroline, an analysis was conducted in 797 patients with ABSSSI (such as deep/extensive cellulitis or a wound infection [surgical or traumatic]) for whom the treatment effect of antibacterials may be supported by historical evidence. This analysis evaluated responder rates based on achieving both cessation of lesion spread and absence of fever on Study Day 3 in the following subgroup of patients:

Patients with lesion size ≥ 75 cm^2 and having one of the following infection types:

- Major abscess with ≥ 5 cm of surrounding erythema
- Wound infection
- Deep/extensive cellulitis

The results of this analysis are shown in Table 9.

Table 9: Clinical Responders at Study Day 3 from Two Adult Phase 3 ABSSSI Trials
 | Teflaro n/N (%) | Vancomycin/ Aztreonam n/N (%) | Treatment Difference (2-sided 95% CI)
ABSSSI Trial 1 | 148/200 (74.0) | 135/209 (64.6) | 9.4 (0.4, 18.2)
ABSSSI Trial 2 | 148/200 (74.0) | 128/188 (68.1) | 5.9 (-3.1, 14.9)

The protocol-specified analyses included clinical cure rates at the Test of Cure (TOC) (visit 8 to 15 days after the end of therapy) in the co-primary CE and MITT populations (Table 10) and clinical cure rates at TOC by pathogen in the Microbiologically Evaluable (ME) population (Table 11). However, there are insufficient historical data to establish the magnitude of drug effect for antibacterial drugs compared with placebo at a TOC time point. Therefore, comparisons of Teflaro to vancomycin plus aztreonam based on clinical response rates at TOC cannot be utilized to establish non-inferiority.

Table 10: Clinical Cure Rates at TOC from Two Adult Phase 3 ABSSSI Trials
 | Teflaro n/N (%) | Vancomycin/ Aztreonam n/N (%) | Treatment Difference (2-sided 95% CI)
Trial 1
CE | 288/316 (91.1) | 280/300 (93.3) | -2.2 (-6.6, 2.1)
MITT | 304/351 (86.6) | 297/347 (85.6) | 1.0 (-4.2, 6.2)
Trial 2
CE | 271/294 (92.2) | 269/292 (92.1) | 0.1 (-4.4., 4.5)
MITT | 291/342 (85.1) | 289/338 (85.5) | -0.4 (-5.8, 5.0)

Table 11: Clinical Cure Rates at TOC by Pathogen from Two Adult Integrated Phase 3 ABSSSI Trials
 | Teflaro n/N (%) | Vancomycin/Aztreonam n/N (%)
Gram-positive: MSSA (methicillin-susceptible) MRSA (methicillin-resistant) | 212/228 (93.0%) 142/152 (93.4%) | 225/238 (94.5%) 115/122 (94.3%)
Streptococcus pyogenes | 56/56 (100%) | 56/58 (96.6%)
Streptococcus agalactiae | 21/22 (95.5%) | 18/18 (100%)
Gram-negative: Escherichia coli | 20/21 (95.2%) | 19/21 (90.5%)
Klebsiella pneumoniae | 17/18 (94.4%) | 13/14 (92.9%)
Klebsiella oxytoca | 10/12 (83.3%) | 6/6 (100%)

Of the 693 patients in the MITT population in the Teflaro arm in the two ABSSSI trials, 20 patients had baseline S. aureus bacteremia (nine MRSA and eleven MSSA). Thirteen of these twenty patients (65%) were clinical responders for ABSSSI at Study Day 3 and 18/20 (90%) were considered clinical success for ABSSSI at TOC.

Pediatric Patients

The ABSSSI pediatric trial was a randomized, parallel-group, active controlled trial in pediatric patients 2 months to < 18 years of age.

A total of 163 children from 2 months to < 18 years of age with clinically documented ABSSSI were enrolled in a randomized, multi-center, multinational, parallel group, active controlled trial comparing Teflaro to vancomycin or cefazolin (each with optional aztreonam). Treatment duration was 5 to 14 days. A switch to oral therapy with either cephalexin, clindamycin, or linezolid after Study Day 3 was allowed. The Modified Intent-to-Treat (MITT) population included all patients who received any amount of study drug according to their randomized treatment group.

The primary objective was to evaluate the safety and tolerability of Teflaro. The study was not powered for comparative inferential efficacy analysis, and no efficacy endpoint was identified as primary.

To evaluate the treatment effect of Teflaro, an analysis was conducted in 159 patients with ABSSSI in the MITT population. This analysis evaluated responder rates based on achieving both cessation of lesion spread and absence of fever on Study Day 3.

The clinical response at Study Day 3 was 80.4% (86/107) for the ceftaroline group and 75.0% (39/52) for the comparator group, with a treatment difference of 5.4% (95% CI of –7.8, 20.3).

Clinical cure rates at test of cure visit (8 to 15 days after the end of therapy) for the ABSSSI pediatric trial were 94.4% (101/107) for Teflaro and 86.5% (45/52) for the comparator, with a treatment difference of 7.9 (95% CI –1.2, 20.2). Indeterminate outcomes occurred at rates of 5.6% (6/107) for the ceftaroline group and 11.5% (6/52) for the comparator group, and rates of clinical failure were 0% (0/107) for the ceftaroline group and 1.9% (1/52) for the comparator group.

The safety and effectiveness of Teflaro were evaluated in a single study that enrolled 11 pediatric patients with a gestational age of ≥34 weeks and a postnatal age of 12 days to less than 2 months of age with known or suspected infections. The majority of patients (8 of 11) received 6 mg/kg Teflaro every 8 hours as an intravenous (IV) infusion over 60 minutes.

14.2 Community-Acquired Bacterial Pneumonia (CABP)

Adult Patients

A total of 1231 adults with a diagnosis of CABP were enrolled in two randomized, multi-center, multinational, double-blind, non-inferiority trials (Trials 1 and 2) comparing Teflaro (600 mg administered IV over 1 hour every 12 hours) with ceftriaxone (1 g ceftriaxone administered IV over 30 minutes every 24 hours). In both treatment groups of CABP Trial 1, two doses of oral clarithromycin (500 mg every 12 hours), were administered as adjunctive therapy starting on Study Day 1. No adjunctive macrolide therapy was used in CABP Trial 2. Patients with known or suspected MRSA were excluded from both trials. Patients with new or progressive pulmonary infiltrate(s) on chest radiography and signs and symptoms consistent with CABP with the need for hospitalization and IV therapy were enrolled in the trials. Treatment duration was 5 to 7 days. A switch to oral therapy was not allowed. Among all subjects who received any amount of study drug in the two CABP trials, the 30-day all-cause mortality rates were 11/609 (1.8%) for the Teflaro group vs. 12/610 (2.0%) for the ceftriaxone group, and the difference in mortality rates was not statistically significant.

To evaluate the treatment effect of ceftaroline, an analysis was conducted in CABP patients for whom the treatment effect of antibacterials may be supported by historical evidence. The analysis endpoint required subjects to meet sign and symptom criteria at Day 4 of therapy: a responder had to both (a) be in stable condition, based on temperature, heart rate, respiratory rate, blood pressure, oxygen saturation, and mental status; (b) show improvement from baseline on at least one symptom of cough, dyspnea, pleuritic chest pain, or sputum production, while not worsening on any of these four symptoms. The analysis used a microbiological intent-to-treat population (mITT population) containing only subjects with a confirmed bacterial pathogen at baseline. Results for this analysis are presented in Table 12.

Table 12: Response Rates at Study Day 4 (72-96 hours) from Two Adult Phase 3 CABP Trials
 | Teflaro n/N (%) | Ceftriaxone n/N (%) | Treatment Difference (2-sided 95% CI)
CABP Trial 1 | 48/69 (69.6%) | 42/72 (58.3%) | 11.2 (-4.6,26.5)
CABP Trial 2 | 58/84 (69.0%) | 51/83 (61.4%) | 7.6 (-6.8,21.8)

The protocol-specified analyses included clinical cure rates at the TOC (8 to 15 days after the end of therapy) in the co-primary Modified Intent-to-Treat Efficacy (MITTE) and CE populations (Table 13) and clinical cure rates at TOC by pathogen in the Microbiologically Evaluable (ME) population (Table 14). However, there are insufficient historical data to establish the magnitude of drug effect for antibacterials drugs compared with placebo at a TOC time point. Therefore, comparisons of Teflaro to ceftriaxone based on clinical response rates at TOC cannot be utilized to establish non-inferiority. Neither trial established that Teflaro was statistically superior to ceftriaxone in terms of clinical response rates. The MITTE population included all patients who received any amount of study drug according to their randomized treatment group and were in PORT (Pneumonia Outcomes Research Team) Risk Class III or IV. The CE population included patients in the MITTE population who demonstrated sufficient adherence to the protocol.

Table 13: Clinical Cure Rates at TOC from Two Adult Phase 3 CABP Trials
 | Teflaro n/N (%) | Ceftriaxone n/N (%) | Treatment Difference (2-sided 95% CI)
CABP Trial 1
CE | 194/224 (86.6%) | 183/234 (78.2%) | 8.4 (1.4, 15.4)
MITTE | 244/291 (83.8%) | 233/300 (77.7%) | 6.2 (-0.2, 12.6)
CABP Trial 2
CE | 191/232 (82.3%) | 165/214 (77.1%) | 5.2 (-2.2, 12.8)
MITTE | 231/284 (81.3%) | 203/269 (75.5%) | 5.9 (-1.0, 12.8)

Table 14: Clinical Cure Rates at TOC by Pathogen from Two Adult Integrated Phase 3 CABP Trials
 | Teflaro n/N (%) | Ceftriaxone n/N (%)
Gram-positive: Streptococcus pneumoniae | 54/63 (85.7%) | 41/59 (69.5%)
Staphylococcus aureus (methicillin-susceptible isolates only) | 18/25 (72.0%) | 14/25 (56.0%)
Gram-negative: Haemophilus influenzae | 15/18 (83.3%) | 17/20 (85.0%)
Klebsiella pneumoniae | 12/12 (100%) | 10/12 (83.3%)
Klebsiella oxytoca | 5/6 (83.3%) | 7/8 (87.5%)
Escherichia coli | 10/12 (83.3%) | 9/12 (75.0%)

Pediatric Patients

The CABP pediatric trial was a randomized, parallel-group, active controlled trial in pediatric patients 2 months to < 18 years of age.

A total of 161 children with a diagnosis of CABP were enrolled in a randomized, multi-center, multinational, active controlled trial comparing Teflaro with ceftriaxone. Patients with new or progressive pulmonary infiltrate(s) on chest radiography and signs and symptoms consistent with CABP including acute onset or worsening symptoms of cough, tachypnea, sputum production, grunting, chest pain, cyanosis, or increased work of breathing with the need for hospitalization and IV therapy were enrolled in the trial. Treatment duration was 5 to 14 days. A switch to oral therapy with amoxicillin clavulanate was allowed on Study Day 4.

The primary objective was to evaluate the safety and tolerability of Teflaro. The study was not powered for comparative inferential efficacy analysis, and no efficacy endpoint was identified as primary.

To evaluate the treatment effect of Teflaro, an analysis was conducted in 143 patients with CABP in the MITT population. This analysis evaluated responder rates at Study Day 4 based on achieving improvement in at least 2 out of 7 symptoms (cough, dyspnea, chest pain, sputum production, chills, feeling of warmth / feverish and exercise intolerance or lethargy) and have worsening in none of these symptoms.

The clinical response at Study Day 4 was 69.2% (74/107) for Teflaro and 66.7% (24/36) for the comparator, with a treatment difference of 2.5% (95% CI of –13.9, 20.9).

Clinical cure rates at test of cure were 87.9% (94/107) for Teflaro and 88.9% (32/36) for the comparator, with a treatment difference of -1.0 (95% CI –11.5, 14.1).

16. HOW SUPPLIED/STORAGE AND HANDLING

Teflaro (ceftaroline fosamil) for injection, a pale yellowish-white to light yellow sterile powder, is supplied in single-dose, clear glass vials containing:

- 600 mg - individual vial (NDC 0456-0600-01) and carton containing 10 vials (NDC 0456-0600-10)
- 400 mg - individual vial (NDC 0456-0400-01) and carton containing 10 vials (NDC 0456-0400-10)

Teflaro vials (unreconstituted) should be stored at 25ºC (77ºF); excursions permitted to 15-30ºC (59-86ºF) [see USP Controlled Room Temperature].

17. PATIENT COUNSELING INFORMATION

- Advise patients that allergic reactions, including serious allergic reactions, could occur and that serious reactions require immediate treatment. They should inform their healthcare provider about any previous hypersensitivity reactions to Teflaro, other beta-lactams (including cephalosporins) or other allergens.
- Advise patients that neurological adverse reactions could occur with Teflaro use. Instruct patients or their caregivers to inform their healthcare provider at once of any neurological signs and symptoms, including encephalopathy (disturbance of consciousness including somnolence, lethargy, confusion, and slow thinking), and seizures for immediate treatment, dosage adjustment, or discontinuation of Teflaro.
- Patients should be counseled that antibacterial drugs including Teflaro should only be used to treat bacterial infections. They do not treat viral infections (e.g., the common cold). When Teflaro is prescribed to treat a bacterial infection, patients should be told that although it is common to feel better early in the course of therapy, the medication should be taken exactly as directed. Skipping doses or not completing the full course of therapy may (1) decrease the effectiveness of the immediate treatment and (2) increase the likelihood that bacteria will develop resistance and will not be treatable by Teflaro or other antibacterial drugs in the future.
- Advise patients that diarrhea is a common problem caused by antibacterial drugs, including Teflaro and usually resolves when the drug is discontinued. Sometimes, frequent watery or bloody diarrhea may occur and may be a sign of a more serious intestinal infection. If severe watery or bloody diarrhea develops, patients should contact their healthcare provider.

Distributed by:
AbbVie Inc.
North Chicago, IL 60064

TEFLARO and its design are trademarks of Allergan Sales, LLC, an AbbVie company.
Baxter® is a registered trademark and Mini-Bag Plus™ is a trademark of Baxter International Inc.

© 2024 AbbVie. All rights reserved.
v6.2USPI0600

PRINCIPAL DISPLAY PANEL

NDC 0456-0400-10
Rx only
Teflaro®
(ceftaroline fosamil) for injection
10 Single-Dose Vials
400 mg/vial
FOR INTRAVENOUS INFUSION ONLY
CONSTITUTED SOLUTION MUST BE
FURTHER DILUTED FOR INTRAVENOUS INFUSION
abbvie

PRINCIPAL DISPLAY PANEL

NDC 0456-0600-10
Rx only
Teflaro®
(ceftaroline fosamil) for injection
10 Single-Dose Vials
600 mg/vial
FOR INTRAVENOUS INFUSION ONLY
CONSTITUTED SOLUTION MUST BE
FURTHER DILUTED FOR INTRAVENOUS INFUSION
abbvie